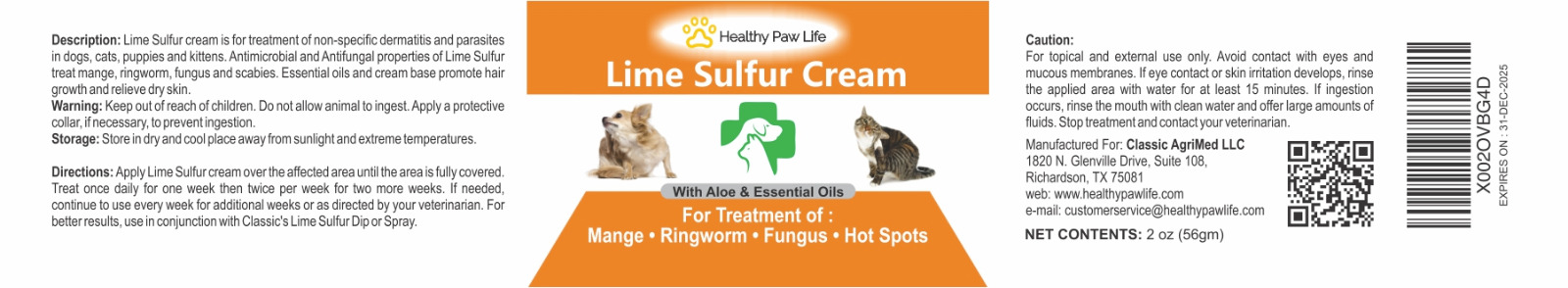 DRUG LABEL: CLASSIC LIME SULFUR
NDC: 86130-301 | Form: CREAM
Manufacturer: CLASSIC AGRIMED LLC
Category: animal | Type: OTC ANIMAL DRUG LABEL
Date: 20231118

ACTIVE INGREDIENTS: CALCIUM POLYSULFIDE 0.16 g/100 g

CLASSIC LIME SULFUR CREAM

Description:
Lime Sulfur cream is for treatment of non-specific dermatitis and parasites in dogs, cats, puppies and kittens. Antimicrobial and Antifungal properties of Lime Sulfur treat mange, ringworm, fungus and scabies. Essential oils and cream base promote hair growth and relieve dry skin.

Warning:
Keep out of reach of children. Do not allow animal to ingest. Apply a protective collar, if necessary, to prevent ingestion.

Storage:
Store in dry and cool place away from sunlight and extreme temperatures.

Directions:
Apply Lime Sulfur cream over the affected area until the area is fully covered. Treat once daily for one week then twice per week for two more weeks. If needed, continue to use every week for additional weeks or as directed by your veterinarian. For better results, use in conjunction with Classic’s Lime Sulfur Dip or Spray.

Caution:
For topical and external use only. Avoid contact with eyes and mucous membranes. If eye contact or skin irritation develops, rinse the applied area with water for at least 15 minutes. If ingestion occurs, rinse the mouth with clean water and offer large amounts of fluids. Stop treatment and contact your veterinarian.

Classic’s Lime Sulfur Cream

With Aloe and Essential Oils

For Treatment Of:

Mange Ringworm Fungus Hot Spots

Manufactured For: Classic Agrimed LLC